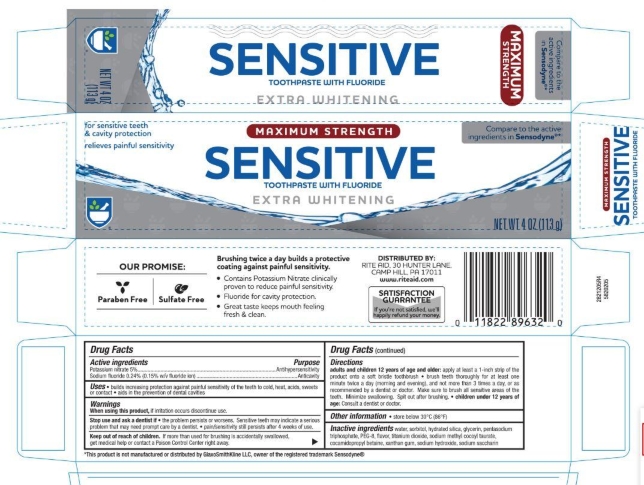 DRUG LABEL: Rite Aid
NDC: 11822-5020 | Form: PASTE, DENTIFRICE
Manufacturer: Rite Aid
Category: otc | Type: HUMAN OTC DRUG LABEL
Date: 20251114

ACTIVE INGREDIENTS: SODIUM FLUORIDE 0.15 g/100 g; POTASSIUM NITRATE 5 g/100 g
INACTIVE INGREDIENTS: WATER; SACCHARIN SODIUM; SODIUM TRIPOLYPHOSPHATE; POLYETHYLENE GLYCOL 400; SORBITOL; TITANIUM DIOXIDE; SODIUM HYDROXIDE; GLYCERIN; XANTHAN GUM; HYDRATED SILICA; COCAMIDOPROPYL BETAINE; SODIUM METHYL COCOYL TAURATE

5820205 Rite Aid Max Str Sensitive Extra Whitening

Drug Facts

Active ingredients

Potassium nitrate 5%

Sodium fluoride 0.24% (0.15% w/v fluoride ion)

Purpose

Antihypersensitivity

Anticavity

Uses

- builds increasing protection against painful sensitivity of the teeth to cold, heat, acids, sweets or contact
- aids in the prevention of dental cavities

Warnings

When using this product do not use longer than 4 weeks unless recommended by a dentist or physician.

STOP USE

See your dentist if the problem worsens. Sensitive teeth may indicate a serious problem that may need prompt care by a dentist.

Keep out of reach of children. If more than used for brushing is accidentally swallowed, get medical help or contact a Poison Control Center right away.

Directions

Adults and children 12 years of age and older: Apply at least a 1-inch strip of the product onto a soft bristle toothbrush

- Brush teeth thoroughly for at least one minute, preferably after each meal or least twice a day (morning and evening) or as recommended by a dentist or physician. Make sure to brush all sensitive areas of the teeth.
- Children under 12 years of age: consult a dentist or physician.

INACTIVE INGREDIENT

Inactive ingredients cocamidopropyl betaine, flavor, glycerin, hydrated silica, PEG-8, sodium hydroxide, sodium methyl cocoyl taurate, sodium saccharin, sodium tripolyphosphate, sorbitol, titanium dioxide, water, xanthan gum

STORAGE AND HANDLING

Store in a cool dry place. Keep tube capped when not in use.

DISTRIBUTED BY:

RITE AID, 30 HUNTER LANE

CAMP HILL, PA 17011

MADE IN USA